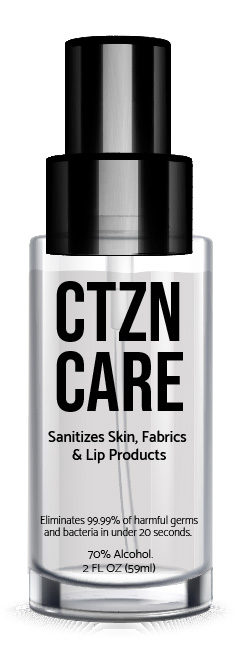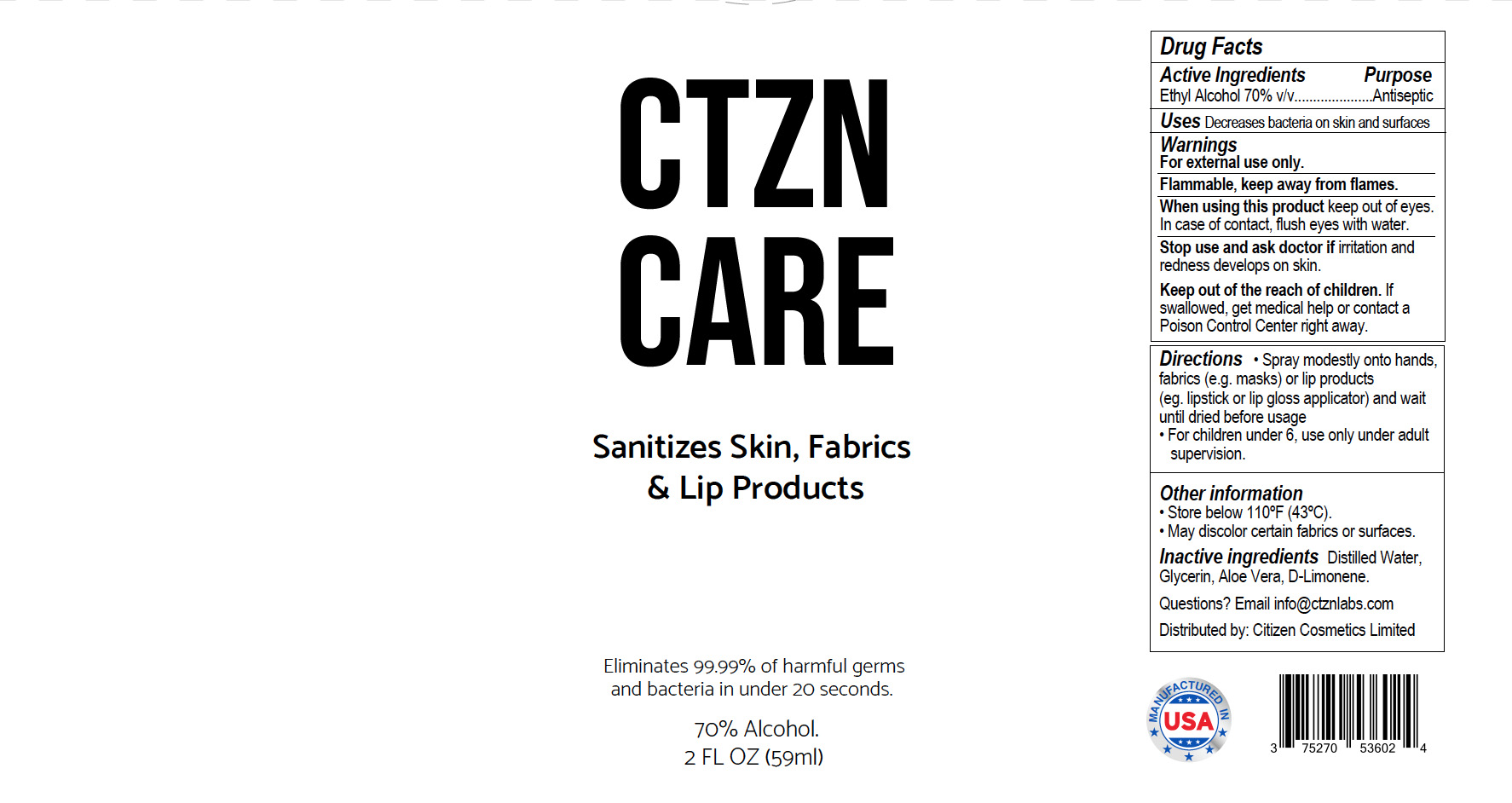 DRUG LABEL: Citizen Sanitizer 70% EtOH
NDC: 75270-536 | Form: SPRAY
Manufacturer: LifeTech Pharma LLC
Category: otc | Type: HUMAN OTC DRUG LABEL
Date: 20200820

ACTIVE INGREDIENTS: ALCOHOL 70 mL/100 mL
INACTIVE INGREDIENTS: GLYCERIN 1.45 mL/100 mL; LIMONENE, (+)- 0.2 mL/100 mL; ALOE VERA LEAF 0.05 mL/100 mL; WATER 28.3 mL/100 mL

Sanitizer Spray

This hand Sanitizer was manufactured according to the Federal Register 21 CFR 310, utilizing:

a. USP/FCC grade Ethyl alcohol 95%

b. Distilled/purified water

c. Glycerin USP/FCC grade

d. Limonene (as fragrance)

e. Aloe Vera extract

Active Ingredient(s)

Ethyl alcohol 70%

Purpose

Antiseptic, Sanitizer Spray.

Uses

Decreases bacteria on skin and surfaces.

Warnings

For external use only. Flammable, keep away from flames.

When using this product keep out of eyes. In case of contact, flush eyes with water.

Stop use section

Stop use and ask doctor if irritation and redness develop.

KEEP OUT OF REACH OF CHILDREN

Keep out of the reach of children. If swallowed, get medical help or contact a Poison Control Center right away.

Directions

• Spray modestly onto hands, fabrics, (e.g. masks) or lip products (eg. lipstick or lip gloss applicator) and wait until dried before usage.

• For children under 6, use only under adult supervision.

Other information

• Store below 110ºF (43ºC).
• May discolor certain fabrics or surfaces.

Inactive ingredients

Inactive ingredients Distilled Water, Glycerin, Aloe Vera, D-Limonene.

Questions

Questions? Email info@ctznlabs.com

Distributed by: Citizen Cosmetics Limited

2 oz Packaging & Label - Principal Display Panel

2 oz Citizen Sanitizer Spray NDC: 75270-536-02